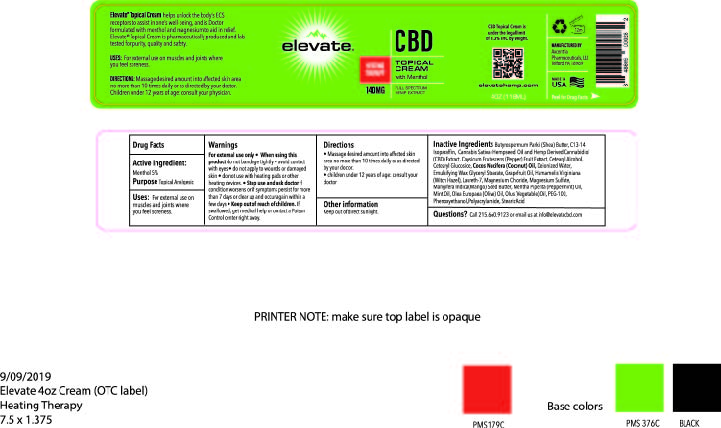 DRUG LABEL: ELEVATE CBD HEATING THERAPY
NDC: 76348-455 | Form: CREAM
Manufacturer: RENU LABORATORIES, INC.
Category: otc | Type: HUMAN OTC DRUG LABEL
Date: 20220113

ACTIVE INGREDIENTS: MENTHOL 5.6 g/112 g
INACTIVE INGREDIENTS: C13-14 ISOPARAFFIN; PEPPERMINT OIL; WHITE WAX; CETOSTEARYL ALCOHOL; SHEA BUTTER; PHENOXYETHANOL; MAGNESIUM SULFATE, UNSPECIFIED; COCONUT OIL; WATER; POLYACRYLAMIDE (10000 MW); MANGIFERA INDICA SEED BUTTER; OLIVE OIL; CANNABIS SATIVA SEED OIL; CANNABIDIOL; STEARIC ACID; CETEARYL GLUCOSIDE; GLYCERYL MONOSTEARATE; LAURETH-7; MAGNESIUM CHLORIDE; WITCH HAZEL; CORN OIL; PEG-100 STEARATE; TABASCO PEPPER

ELEVATE CBD HEATING THERAPY

ACTIVE INGREDIENT

Menthol 5%

Stop use and ask doctor if condition worsens or if symptoms persist for more than 7 days or clear up and occur again within a few days

Warnings

For external use only

- When using this product do not bandage tightly
- avoid contact with eyes
- do not apply to wounds or damaged skin
- do not use with heating pads or other heating devices.
- Stop use and ask doctor if condition worsens or if symptoms persist for more than 7 days or clear up and occur again within a few days
- Keep out of reach of children. If swallowed, get medical help or contact a Poison Control Center right away.

Keep out of reach of children.

When using this product do not bandage tightly

- avoid contact with eyes
- do not apply to wounds or damaged skin
- do not use with heating pads or other heating devices.

Purpose

Topical Analgesic

QUESTIONS

Questions? Call 215.660.9123 or email us at info@elevatecbd.com

INDICATIONS AND USAGE

Uses: For external use on muscles and joints where you feel soreness.

Directions

- Massage desired amount into affected skin area no more than 10 times daily or as directed by your doctor.
- children under 12 years of age: consult your doctor

Other information

Keep out of direct sunlight.

INACTIVE INGREDIENT

Butyrospermum Parkii (Shea) Butter, C13-14 Isoparaffin, Cannabis Sativa (Hempseed) Oil and Hemp Derived Cannabidiol (CBD) Extract, Cetearyl Alcohol, Cetearyl Glucoside, Cocos Nucifera (Coconut) Oil, Deionized Water, Emusifying Wax, Glyceryl Stearate, Grapefruit Oil, Hamamelis Virginiana (Witch Hazel), Laureth-7, Magnesium Chloride, Magnesium Sulfate, Mangifera Indica (Mango) Seed Butter, Mentha Piperita (Peppermint) Oil, Mint Oil, Olea Europaea (Olive) Oil, Olus (Vegetable) Oil, PEG-100, Phenoxyethanol, Polyacrylamide, Stearic Acid

DESCRIPTION

Elevate Topical Cream helps unlock the body's ECS receptors to assist in one's well being and is Doctor formulated with menthol and magnesium to aid in relief. Elevate Topical Cream is pharmaceutically produced and lab tested for purity, quality and safety.

ELEVATE HEATING THERAPY TOPICAL CREAM LABEL